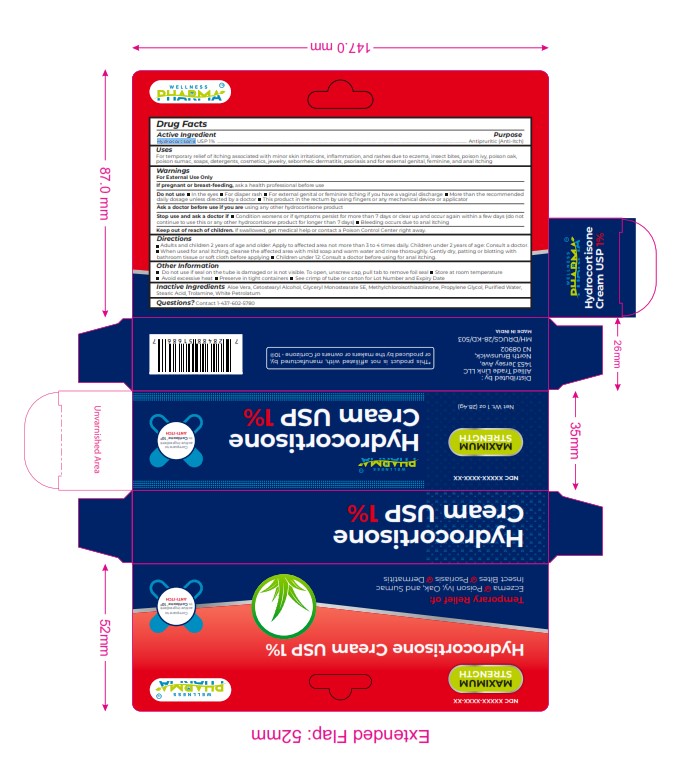 DRUG LABEL: HYDROCORTISONE
NDC: 84387-005 | Form: CREAM
Manufacturer: ALLIED TRADE LINK LLC
Category: otc | Type: HUMAN OTC DRUG LABEL
Date: 20241112

ACTIVE INGREDIENTS: HYDROCORTISONE 10 mg/1 g
INACTIVE INGREDIENTS: ALOE VERA LEAF; PROPYLENE GLYCOL; WATER; GLYCERYL STEARATE SE; METHYLCHLOROISOTHIAZOLINONE; STEARIC ACID; WHITE PETROLATUM; CETOSTEARYL ALCOHOL; TROLAMINE

HYDROCORTISONE

Purpose
Hydrocortisone USP 1% ............................................................................................................................................................................................................................................ Antipruritic (Anti-Itch)
Uses
For temporary relief of itching associated with minor skin irritations, inﬂammation, and rashes due to eczema, insect bites, poison ivy, poison oak,
poison sumac, soaps, detergents, cosmetics, jewelry, seborrheic dermatitis, psoriasis and for external genital, feminine, and anal itching

WARNINGS

For External Use Only
If pregnant or breast-feeding, ask a health professional before use
Do not use In the eyes For diaper rash For external genital or feminine itching if you have a vaginal discharge More than the recommended
daily dosage unless directed by a doctor This product in the rectum by using ﬁngers or any mechanical device or applicator
Ask a doctor before use if you are using any other hydrocortisone product
Stop use and ask a doctor if Condition worsens or if symptoms persist for more than 7 days or clear up and occur again within a few days (do not
continue to use this or any other hydrocortisone product for longer than 7 days) Bleeding occurs due to anal itching

INACTIVE INGREDIENT

nactive Ingredients Aloe Vera, Cetostearyl Alcohol, Glyceryl Monostearate SE, Methylchloroisothiazolinone, Propylene Glycol, Puriﬁed Water, Stearic Acid, Trolamine, White Petrolatum

INDICATIONS AND USAGE

For temporary relief of itching associated with minor skin irritations, inﬂammation, and rashes due to eczema, insect bites, poison ivy, poison oak, poison sumac, soaps, detergents, cosmetics, jewelry, seborrheic dermatitis, psoriasis and for external genital, feminine, and anal itching

Keep out of reach of children. If swallowed, get medical help or contact a Poison Control Center right away.

PURPOSE

antipruritic (Anti-Itch